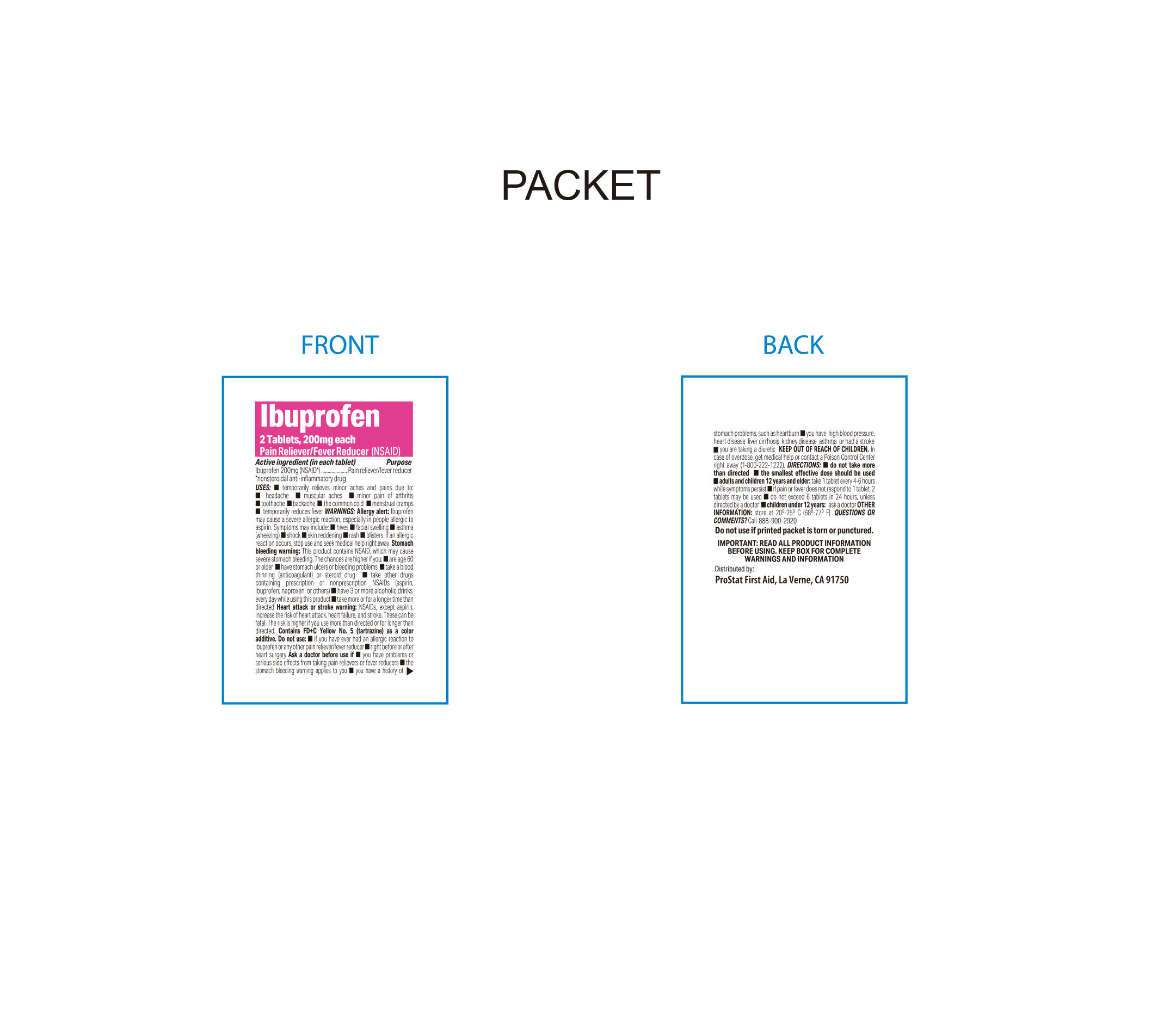 DRUG LABEL: Ibuprofen
NDC: 58228-6185 | Form: TABLET
Manufacturer: PROSTAT FIRST AID
Category: otc | Type: HUMAN OTC DRUG LABEL
Date: 20250807

ACTIVE INGREDIENTS: IBUPROFEN 200 mg/1 1
INACTIVE INGREDIENTS: FD&C BLUE NO. 2; MAGNESIUM STEARATE; LECITHIN, SOYBEAN; CROSCARMELLOSE SODIUM; POLYETHYLENE GLYCOL 4000; FD&C YELLOW NO. 5; POLYVINYL ALCOHOL, UNSPECIFIED; MICROCRYSTALLINE CELLULOSE; SILICON DIOXIDE; STARCH, CORN; TALC; FD&C YELLOW NO. 6; FERRIC OXIDE RED; TITANIUM DIOXIDE

ProStat Ibuprofen Tablets 200mg

Active Ingredient (in each tablet)

Ibuprofen, 200mg (NSAID*)

*nonsteroidal anti-inflammatory drug

Purpose

Pain Releiver / Fever Reducer

nonsteroidal anti-inflammatory drug

Do Not Use

- If you have ever had an allergic reaction to ibuprofen or any other pain reliever/fever reducer
- right before or after heart surgery

Uses

Temporarily relieves minor aches and pains due to

- Common cold
- headache
- minor pain of arthritis
- toothache
- backache
- muscular aches
- menstrual cramps

temporarily reduces fever

Warnings

Allergy alert

Ibuprofen may cause severe allergic reactions, especially in people allergic to aspirin. Symptoms may include

- hives
- facial swelling
- asthma (wheezing)
- shock
- skin reddening
- rash
- blisters

if an allergic reaction occurs, stop use and seek medical help right away

Stomach Bleeding Warning

This product contains a NSAID, which may cause severe stomach bleeding. The chances are higher if you:

- are age 60 or older
- have stomach ulcers or bleeding problems
- take blood thinning (anticoagulant) or steroid drug
- take other drugs containing prescription or nonprescription NSAIDs (aspirin, ibuprofen, naproxen or others)
- have 3 or more alcoholic drinks every day while using this product
- take more or for a longer time than directed

Heart attack or stroke warning

NSAIDs, except aspirin, increase the risk of heart attack, heart failure, and stroke. These can be fatal. The risk is higher if you use more than directed or for longer than directed.

Contains FD+C Yellow No. 5 (tartrazine) as a color additive

Ask a doctor before use if

- You have problems or serious side effects from taking pain relievers or fever reducers
- the stomach bleeding warning applies to you
- you have a history of stomach problems, such as heartburn
- you have high blood pressure, heart disease, liver cirrhosis, kidney disease, asthma, or had a stroke
- you are taking a diuretic

Ask a doctor or pharmacist before use if you are

- Taking aspirin for heart attack or stroke, because ibuprofen may decrease the benefit of aspirin
- under a doctor's care for any serious condition
- taking any other drug

Keep out of reach of children. In case of overdose, get medical help or contact a Poison Control Center right away (1-800-222-1222).

Directions

- Do not take more than directed.
- The smallest effective dose should be used

Adults and children 12 years and older

- Take 1 tablet every 4-6 hours while symptoms persist
- If pain or fever does not respond to 1 tablet, 2 tablets may be used
- Do not exceed 6 tablets in 24 hours, unless directed by a doctor

Children under 12 years of age

- Ask a doctor

Stop Use and ask a doctor if

You experience any of the following signs of stomach bleeding:

- feel faint
- vomit blood
- have bloody or black stools
- have stomach pain that does not get better

You have symptoms of heart problems or stroke

- chest pain
- trouble breathing
- weakness in one part or side of body
- slurred speech
- leg swelling

- Pain gets worse or lasts more than 10 days
- Fever gets worse or lsats more than 3 days
- redness or swelling is present in the painful area
- any new symptoms appear

If pregnant or breast-feeding

Ask a health professional before use. It is especially important not to use ibuprofen during the last 3 months of pregnancy unless definitely directed to do so by a doctor because it may cause problems in the unborn child or complications during delivery.

Other Information

- Store at 20ºC - 25ºC (68ºF - 77ºF)
- Do not use if printed packet is torn or punctured.

TAMPER EVIDENTchild resistant packets. Do not use any opened or torn packets.

Inactive Ingredients

Colloidal Silicon Dioxide, Croscarmellose Sodium, FD&C Blue #2, FD&C Yellow #5, FD&C Yellow #6, Iron Oxide Red, Lecithin, Magnesium Stearate, Microcrystalline Cellulose, Polyethylene Glycol, Polyvinyl Alcohol, Pregelatinized Starch, Talc, Titanium Dioxide

Questions or Comments?

Call 1-888-900-2920

IMPORTANT: READ ALL PRODUCT INFORMATION BEFORE USING. KEEP BOX FOR COMPLETE WARNINGS AND INFORMATION.

When using this product

Take with food or milk if stomach upset occurs

Distributed By:

ProStat First Aid

La Verne, CA. USA

1-888-900-2920

*This product is not manufactured or distributed by Pfizer, owner of the registered trademark Advil®

Made in the USA